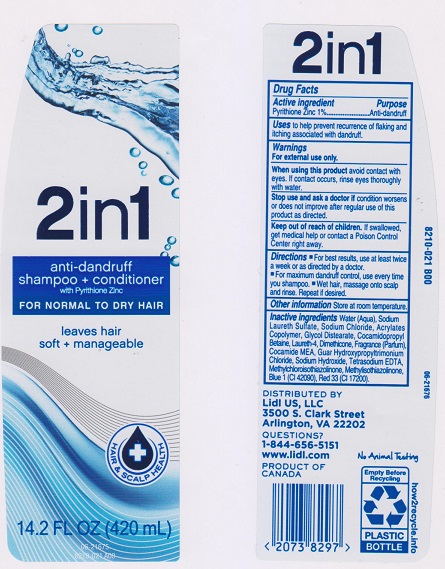 DRUG LABEL: 2 in 1 Antidandruff
NDC: 63148-415 | Form: SHAMPOO
Manufacturer: Apollo Health and Beauty Care Inc.
Category: otc | Type: HUMAN OTC DRUG LABEL
Date: 20170330

ACTIVE INGREDIENTS: PYRITHIONE ZINC 10 mg/1 mL
INACTIVE INGREDIENTS: WATER; SODIUM LAURETH SULFATE; SODIUM CHLORIDE; METHACRYLIC ACID - METHYL METHACRYLATE COPOLYMER (1:1); GLYCOL DISTEARATE; COCAMIDOPROPYL BETAINE; LAURETH-4; DIMETHICONE; COCO MONOETHANOLAMIDE; GUAR HYDROXYPROPYLTRIMONIUM CHLORIDE (1.7 SUBSTITUENTS PER SACCHARIDE); SODIUM HYDROXIDE; EDETATE SODIUM; METHYLCHLOROISOTHIAZOLINONE; METHYLISOTHIAZOLINONE; FD&C BLUE NO. 1; D&C RED NO. 33

Drug Facts

Active ingredient

Pyrithione Zinc 1%

Purpose

Anti-dandruff

Uses

To help prevent recurrence of flaking and itching associated with dandruff.

Warnings

For external use only.

When using this product

avoid contact with eyes, If contact occurs, rinse eyes thoroughly with water.

Stop use and ask a doctor if

condition worsens or does not improve after regular use of this product as directed.

Keep out of reach of children.

If swallowed, get medical help or contact a Poison Control Center immediately.

Directions

- For best results, use at least twice a week or as directed by a doctor.
- For maximum dandruff control, use every time you shampoo.
- Wet hair, massage onto scalp and rinse. Repeat if desired.

Other information

Store at room temperature.

Inactive ingredients

Water (Aqua), Sodium Laureth Sulfate, Sodium Chloride, Acrylates Copolymer, Glycol Distearate, Cocamidopropyl Betaine, Laureth-4, Dimethicone, Fragrance (Parfum), Cocamide MEA, Guar Hydroxypropyltrimonium Chloride, Sodium Hydroxide, Tetrasodium EDTA, Methylchloroisothiazolinone, Methylisothiazolinone, Blue 1 (CI 42090), Red 33 (CI 17200).